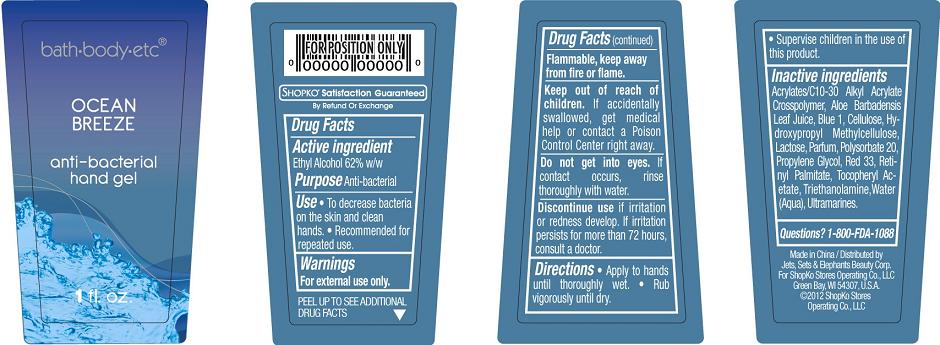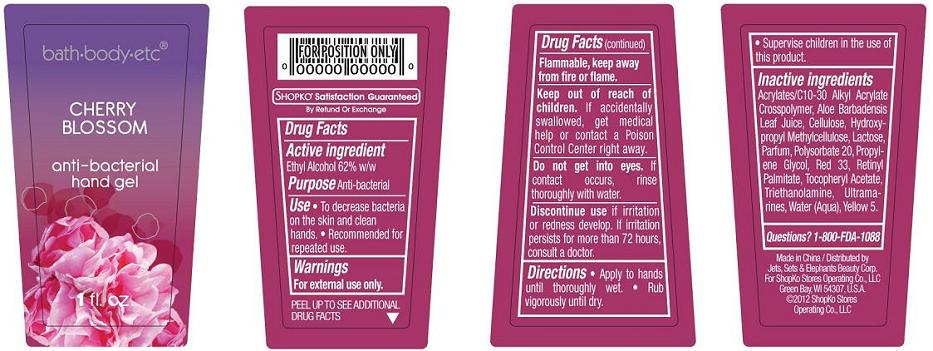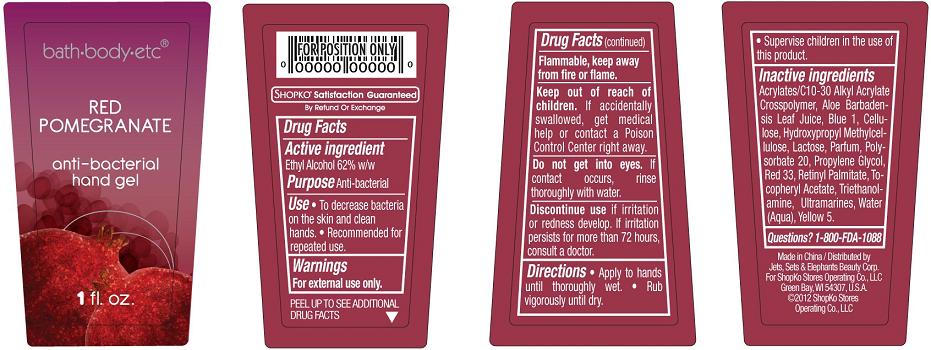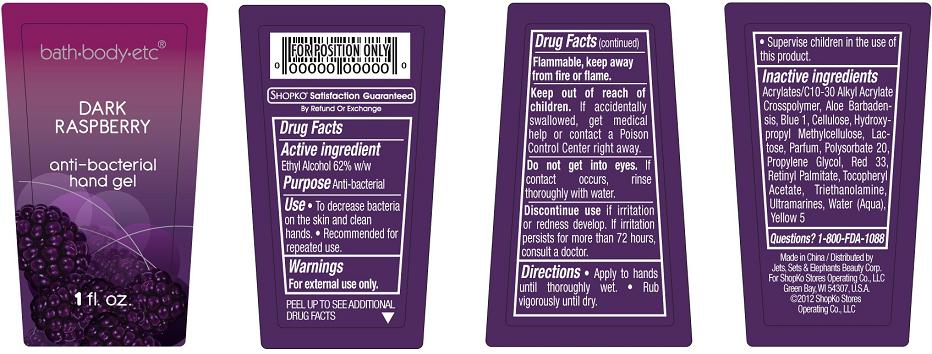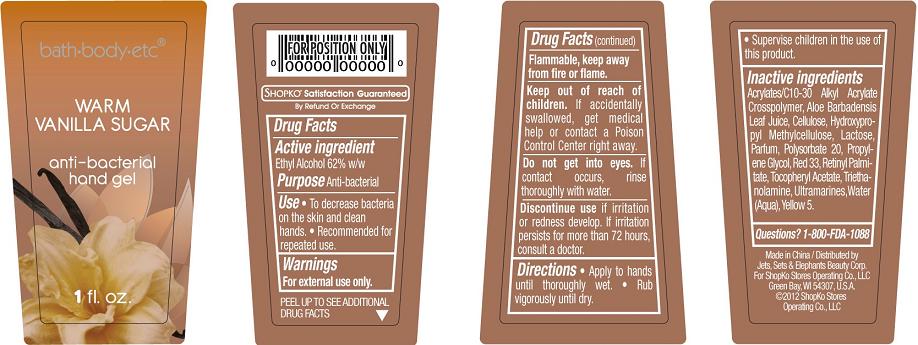 DRUG LABEL: Shopko Antibacterial Hand Sanitizer
NDC: 50988-288 | Form: GEL
Manufacturer: Jets, Sets, & Elephants Beauty Corp.
Category: otc | Type: HUMAN OTC DRUG LABEL
Date: 20120628

ACTIVE INGREDIENTS: ALCOHOL 0.62 mL/1 mL
INACTIVE INGREDIENTS: WATER; PROPYLENE GLYCOL; ALOE VERA LEAF; CARBOMER INTERPOLYMER TYPE A (55000 MPA.S); POLYSORBATE 20; TROLAMINE; VITAMIN A PALMITATE; LACTOSE; CELLULOSE, MICROCRYSTALLINE; HYPROMELLOSE 2208 (100 MPA.S); .ALPHA.-TOCOPHEROL ACETATE; ULTRAMARINE BLUE; D&C RED NO. 33; FD&C BLUE NO. 1

SHOPKO® Antibacterial Hand Sanitizer - Ocean Breeze, Cherry Blossom, Red Pomegranate, Dark Raspberry, and Warm Vanilla Sugar

Active Ingredient

Ethyl Alcohol 62% w/w

Purpose

Anti-bacterial

Use

- To decrease bacteria on the skin and clean hands.
- Recommended for repeated use.

Warnings

For external use only.

Flammable, keep away from fire or flame.

Keep out of reach of children.

If accidentally swallowed, get medical help or contact a Poison Control Center right away.

Do not get into eyes.

If contact occurs, rinse thoroughly with water.

Discontinue use

if irritation or redness develop. If irritation persists for more than 72 hours, consult a doctor.

Directions

- Apply to hands until thoroughly wet.
- Rub vigorously until dry.
- Supervise children in the use of this product.

Inactive ingredients (Ocean Breeze)

Acrylates/C10-30 Alkyl Acrylate Crosspolymer, Aloe Barbadensis Leaf Juice, Aqua, Blue 1, Cellulose, Hydroxypropyl Methylcellulose, Lactose, Parfum, Polysorbate 20, Propylene Glycol, Red 33, Retinyl Palmitate, Tocopheryl Acetate, Triethanolamine, and Ultramarines

Inactive ingredients (Cherry Blossom)

Acrylates/C10-30 Alkyl Acrylate Crosspolymer, Aloe Barbadensis Leaf Juice, Aqua, Cellulose, Hydroxypropyl Methylcellulose, Lactose, Parfum, Polysorbate 20, Propylene Glycol, Red 40, Retinyl Palmitate, Tocopheryl Acetate, Triethanolamine, Ultramarines, Yellow 5

Inactive ingredients (Red Pomegranate)

Acrylates/C10-30 Alkyl Acrylate Crosspolymer, Aloe Barbadensis Leaf Juice, Aqua, Blue 1, Cellulose, Hydroxypropyl Methylcellulose, Lactose, Parfum, Polysorbate 20, Propylene Glycol, Red 33, Retinyl Palmitate, Tocopheryl Acetate, Triethanolamine, Ultramarines, Yellow 5

Inactive ingredients (Dark Raspberry)

Acrylates/C10-30 Alkyl Acrylate Crosspolymer, Aloe Barbadensis Leaf Juice, Aqua, Blue 1, Cellulose, Hydroxypropyl Methylcellulose, Lactose, Parfum, Polysorbate 20, Propylene Glycol, Red 33, Retinyl Palmitate, Tocopheryl Acetate, Triethanolamine, Ultramarines, Yellow 5

Inactive ingredients (Warm Vanilla Sugar)

Acrylates/C10-30 Alkyl Acrylate Crosspolymer, Aloe Barbadensis Leaf Juice, Aqua, Cellulose, Hydroxypropyl Methylcellulose, Lactose, Parfum, Polysorbate 20, Propylene Glycol, Red 40, Retinyl Palmitate, Tocopheryl Acetate, Triethanolamine, Ultramarines, Yellow 5

QUESTIONS?

1-800-FDA-1088

PACKAGE/LABEL PRINCIPAL DISPLAY PANEL

bath·body·etc®

Ocean Breeze

anti-bacterial hand gel

1 fl. oz.

Made in China
Distributed by Jets, Sets & Elephants Beauty Corp,
For ShopKo Stores Operating Co., LLC
Green Bay, WI 54307, U.S.A
©2012 ShopKo Stores Operating Co., LLC

Ocean Breeze

PACKAGE/LABEL PRINCIPAL DISPLAY PANEL

bath·body·etc®

Cherry Blossom

anti-bacterial hand gel

1 fl. oz.

Made in China
Distributed by Jets, Sets & Elephants Beauty Corp,
For ShopKo Stores Operating Co., LLC
Green Bay, WI 54307, U.S.A
©2012 ShopKo Stores Operating Co., LLC

Cherry Blossom

PACKAGE/LABEL PRINCIPAL DISPLAY PANEL

bath·body·etc®

Red Pomegranate

anti-bacterial hand gel

1 fl. oz.

Made in China
Distributed by Jets, Sets & Elephants Beauty Corp,
For ShopKo Stores Operating Co., LLC
Green Bay, WI 54307, U.S.A
©2012 ShopKo Stores Operating Co., LLC

Red Pomegranate

PACKAGE/LABEL PRINCIPAL DISPLAY PANEL

bath·body·etc®

Dark Raspberry

anti-bacterial hand gel

1 fl. oz.

Made in China
Distributed by Jets, Sets & Elephants Beauty Corp,
For ShopKo Stores Operating Co., LLC
Green Bay, WI 54307, U.S.A
©2012 ShopKo Stores Operating Co., LLC

Dark Raspberry

PACKAGE/LABEL PRINCIPAL DISPLAY PANEL

bath·body·etc®

Warm Vanilla Sugar

anti-bacterial hand gel

1 fl. oz.

Made in China
Distributed by Jets, Sets & Elephants Beauty Corp,
For ShopKo Stores Operating Co., LLC
Green Bay, WI 54307, U.S.A
©2012 ShopKo Stores Operating Co., LLC

Warm Vanilla Sugar